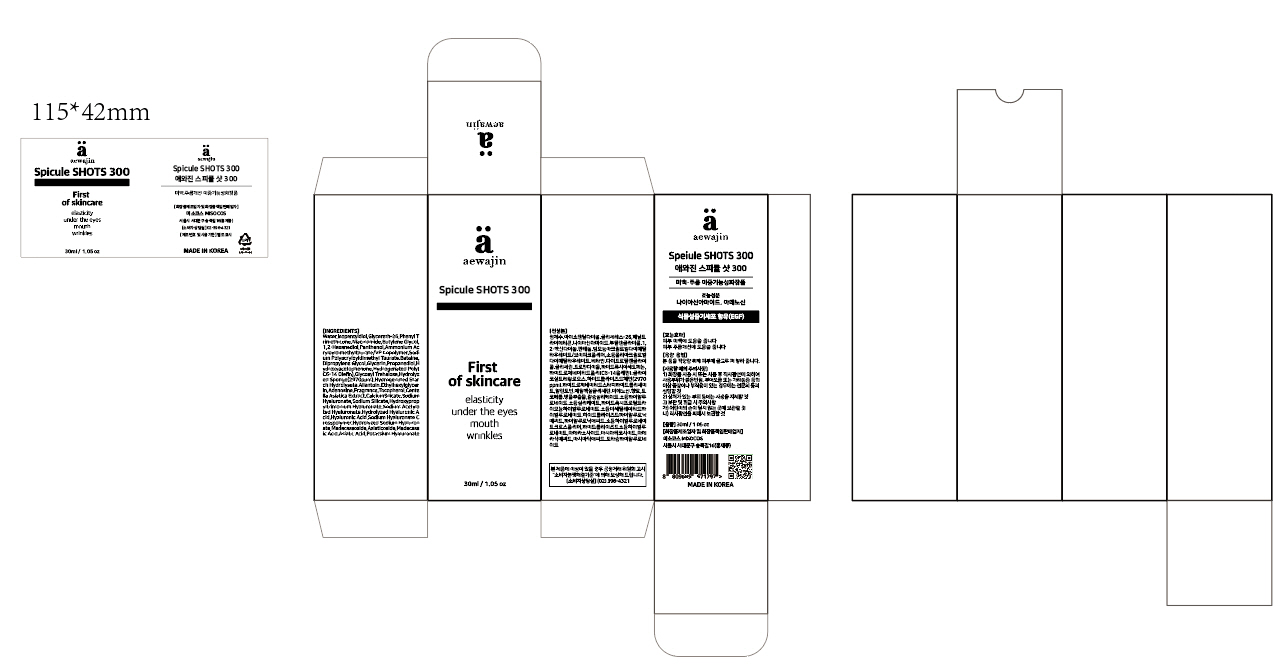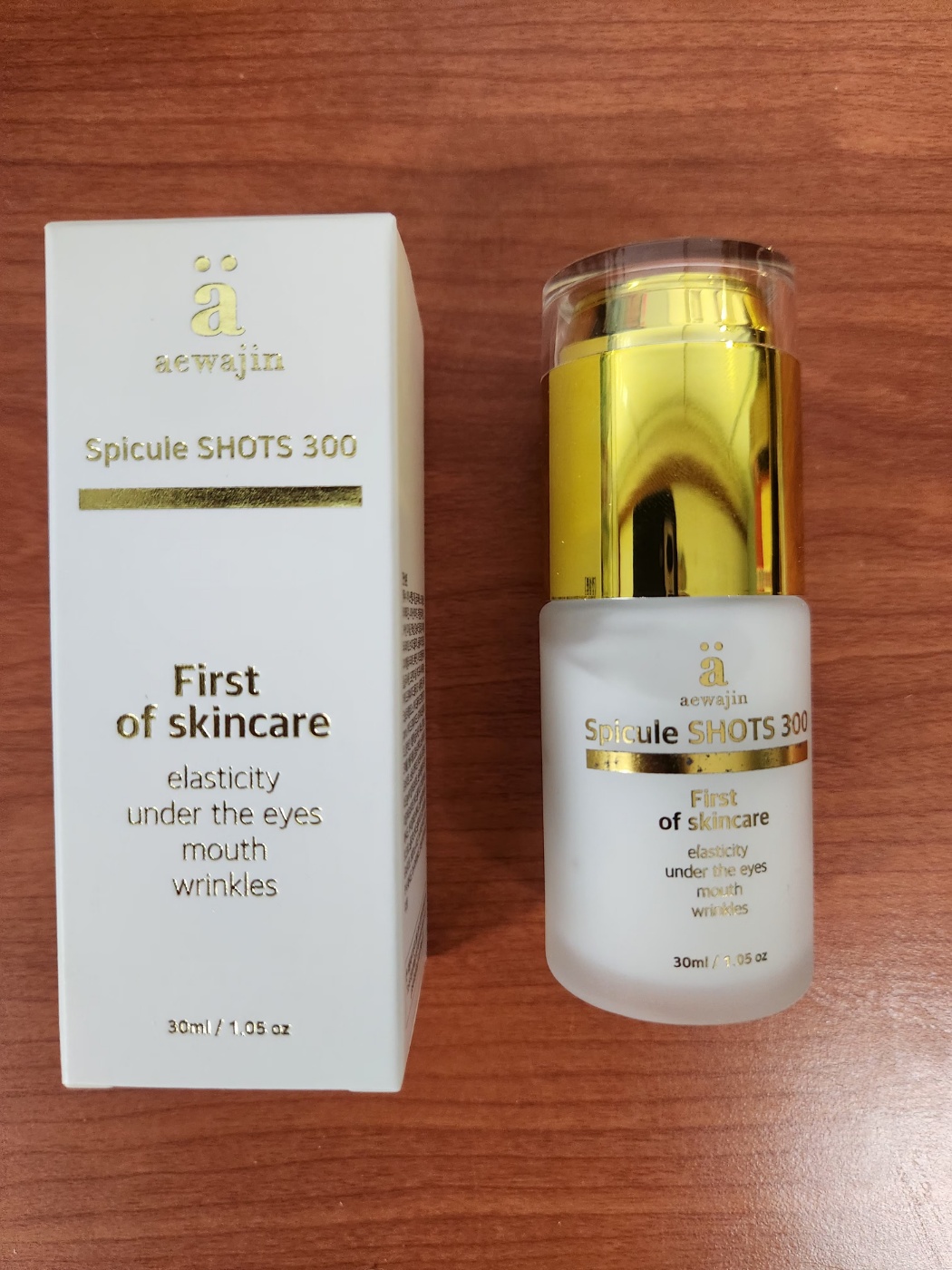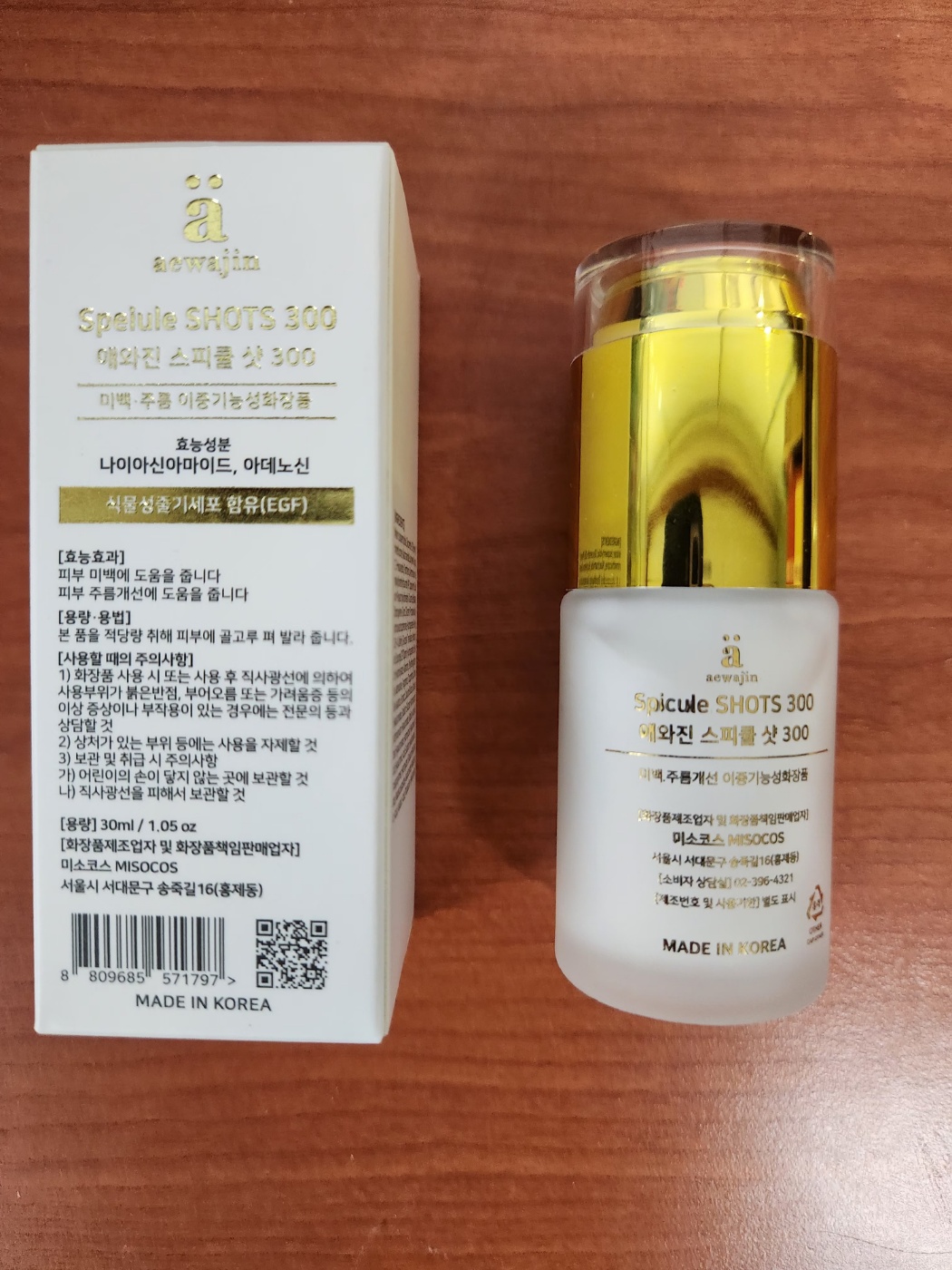 DRUG LABEL: aewajin Spicule SHOTS 300
NDC: 73466-0010 | Form: LIQUID
Manufacturer: MISOCOS
Category: otc | Type: HUMAN OTC DRUG LABEL
Date: 20250613

ACTIVE INGREDIENTS: NIACINAMIDE 2 g/100 mL; ADENOSINE 0.04 g/100 mL
INACTIVE INGREDIENTS: WATER; ALLANTOIN

Drug Facts

ACTIVE INGREDIENT

Niacinamide

Adenosine

INACTIVE INGREDIENT

Water
Isopentyldiol
Glycereth-26
Phenyl Trimethicone
Butylene Glycol
1,2-Hexanediol
Panthenol
Ammonium Acryloyldimethyltaurate/VP Copolymer
Sodium Polyacryloyldimethyl Taurate
Betaine
Dipropylene Glycol
Glycerin
Propanediol
Hydroxyacetophenone
Hydrogenated Poly(C6-14 Olefin)
Glycosyl Trehalose
Hydrolyzed Sponge
Hydrogenated Starch Hydrolysate
Allantoin
Ethylhexylglycerin
Fragrance
Tocopherol
Centella Asiatica Extract
Calcium Silicate
Sodium Hyaluronate
Sodium Silicate
Hydroxypropyltrimonium Hyaluronate
Sodium Acetylated Hyaluronate
Hydrolyzed Hyaluronic Acid
Hyaluronic Acid
Sodium Hyaluronate Crosspolymer
Hydrolyzed Sodium Hyaluronate
Madecassoside
Asiaticoside
Madecassic Acid
Asiatic Acid
Potassium Hyaluronate

PURPOSE

skin protectant

keep out of reach of the children

INDICATIONS AND USAGE

take a suitable amount on the skin

WARNINGS

■ if following abnormal symptoms occurs after use , stop use and consult with a skin specialist

red specks, swelling, itching

■ don’t use on the part where there is injury, eczema, or dermatitis

Keep out of reach of children

■ if swallowed, get medical help or contact a person control center immediately

DOSAGE AND ADMINISTRATION

for external use only